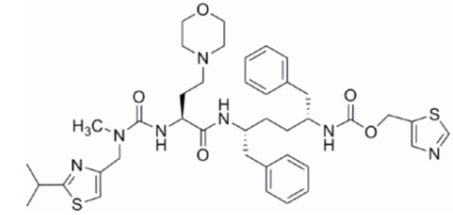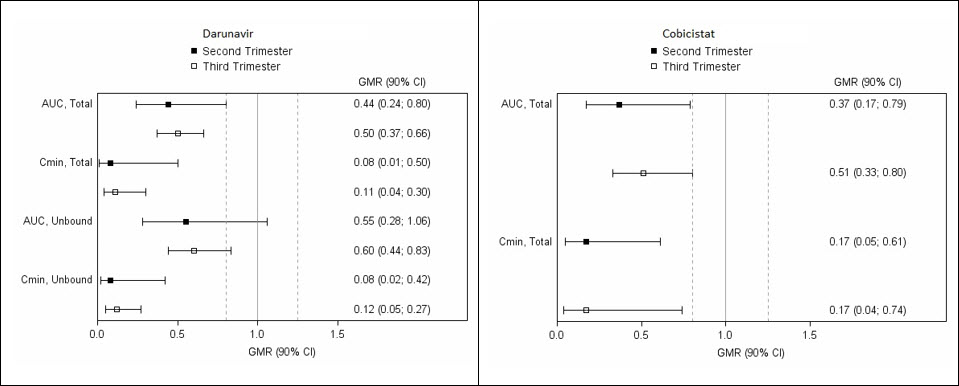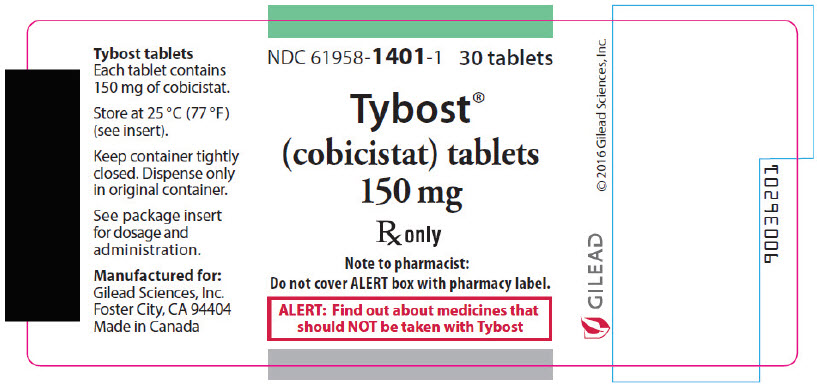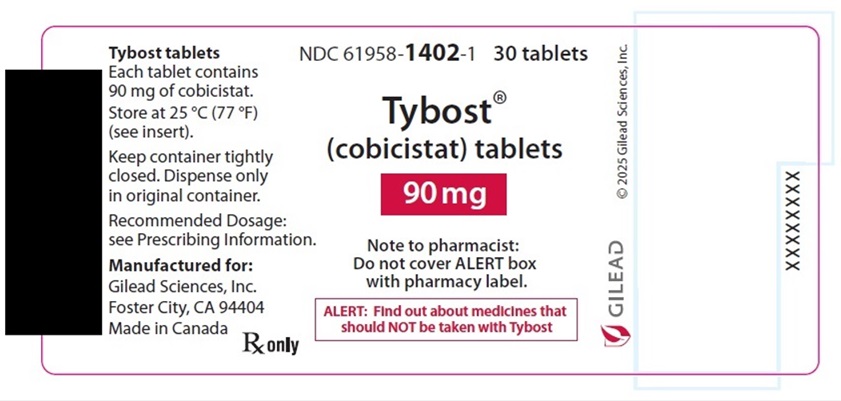 DRUG LABEL: Tybost
NDC: 61958-1401 | Form: TABLET, FILM COATED
Manufacturer: Gilead Sciences, Inc.
Category: prescription | Type: HUMAN PRESCRIPTION DRUG LABEL
Date: 20260210

ACTIVE INGREDIENTS: COBICISTAT 150 mg/1 1
INACTIVE INGREDIENTS: CROSCARMELLOSE SODIUM; MAGNESIUM STEARATE; MICROCRYSTALLINE CELLULOSE; WATER; POLYVINYL ALCOHOL, UNSPECIFIED; TITANIUM DIOXIDE; POLYETHYLENE GLYCOL 3350; TALC; FD&C YELLOW NO. 6; FERRIC OXIDE YELLOW

HIGHLIGHTS OF PRESCRIBING INFORMATION

These highlights do not include all the information needed to use TYBOST safely and effectively. See full prescribing information for TYBOST.
TYBOST® (cobicistat) tablets, for oral use
Initial U.S. Approval: 2012

RECENT MAJOR CHANGES

Indications and Usage (1.1) | 06/2025
Dosage and Administration (2.2) | 06/2025

1 INDICATIONS AND USAGE

TYBOST is a CYP3A inhibitor indicated to increase systemic exposure of atazanavir or darunavir (once daily dosing regimen) in combination with other antiretroviral agents in the treatment of HIV-1 infection in adults and in pediatric patients weighing at least 14 kg. (1.1)

Limitations of Use:

- TYBOST is not interchangeable with ritonavir to increase systemic exposure of darunavir 600 mg twice daily, fosamprenavir, saquinavir, or tipranavir due to lack of exposure data. The use of TYBOST is not recommended with darunavir 600 mg twice daily, fosamprenavir, saquinavir, or tipranavir. (1.2, 5.4)
- Complex or unknown mechanisms of drug interactions preclude extrapolation of ritonavir drug interactions to certain TYBOST interactions. TYBOST and ritonavir when administered with either atazanavir or darunavir may result in different drug interactions when used with concomitant medications. (1.2, 5.3, 7, 12.3)

2 DOSAGE AND ADMINISTRATION

- TYBOST must be coadministered with atazanavir or darunavir at the same time, with food, and in combination with other HIV-1 antiretroviral agents. (2.1, 2.2)
- Recommended dosage in adults: (2.1)

Adult Patient Populations | Coadministered Agent Dosage | TYBOST Dosage
Treatment-naïve or treatment-experienced | atazanavir 300 mg orally once daily | 150 mg orally once daily
Treatment-naïve or treatment-experienced with no darunavir resistance-associated substitutions | darunavir 800 mg orally once daily | 150 mg orally once daily

- Recommended dosage in pediatric patients: TYBOST 150 mg or TYBOST 90 mg orally once daily based on body weight. For dosage recommendations for TYBOST and the coadministered protease inhibitor atazanavir or darunavir in pediatric patients, refer to Table 2 and Table 3 of the full prescribing information respectively. (2.2)
- Prior to starting TYBOST, assess estimated creatinine clearance. (2.3)
- Coadministration with tenofovir disoproxil fumarate (TDF): assess estimated creatinine clearance, urine glucose, and urine protein at baseline. (2.3)
- TYBOST coadministered with TDF is not recommended in patients who have an estimated creatinine clearance below 70 mL/min because dose adjustment of TDF is required below 50 mL/min and such dose adjustments have not been established for coadministration with TYBOST. (2.4)

3 DOSAGE FORMS AND STRENGTHS

Tablets: 150 mg and 90 mg. (3)

4 CONTRAINDICATIONS

Coadministration with certain drugs for which altered plasma concentrations are associated with serious and/or life-threatening events or loss of therapeutic effect. (4)

5 WARNINGS AND PRECAUTIONS

- Assess creatinine clearance (CLcr) before initiating treatment. (5.1)
- When TYBOST is used in combination with a TDF-containing regimen, cases of acute renal failure and Fanconi syndrome have been reported. (5.2)
- Use with TDF: Assess urine glucose and urine protein at baseline and monitor CLcr, urine glucose, and urine protein. Monitor serum phosphorus in patients with or at risk for renal impairment. (5.2)
- TYBOST in combination with more than one antiretroviral that requires pharmacokinetic enhancement (i.e., two protease inhibitors or elvitegravir in combination with a protease inhibitor) is not recommended. (5.4)
- Use with HIV-1 protease inhibitors other than atazanavir or darunavir administered once daily is not recommended. (5.4)
- Coadministration with drugs or regimens containing ritonavir is not recommended. (5.4)

6 ADVERSE REACTIONS

The most common adverse drug reactions observed with TYBOST in combination with atazanavir (incidence greater than 5%, Grades 2−4) are jaundice and rash. (6.1)

To report SUSPECTED ADVERSE REACTIONS, contact Gilead Sciences, Inc. at 1-800-GILEAD-5 or FDA at 1-800-FDA-1088 or www.fda.gov/medwatch.

7 DRUG INTERACTIONS

TYBOST, in combination with atazanavir or darunavir, can alter the concentration of drugs metabolized by CYP3A or CYP2D6. Drugs that induce CYP3A can alter the concentrations of TYBOST, atazanavir and darunavir. Consult the full prescribing information prior to and during treatment for potential drug interactions. (4, 5.3, 7, 12.3)

8 USE IN SPECIFIC POPULATIONS

- Pregnancy: TYBOST coadministered with darunavir or atazanavir is not recommended during pregnancy. TYBOST coadministered with darunavir or atazanavir should not be initiated in pregnant individuals. (2.5, 8.1, 12.3)
- Pediatrics: Not recommended for patients weighing less than 14 kg. (8.4)

FULL PRESCRIBING INFORMATION

1 INDICATIONS AND USAGE

1.1 Indications

Adult Patients:

TYBOST is a CYP3A inhibitor indicated to increase systemic exposure of atazanavir or darunavir (once daily dosing regimen) in combination with other antiretroviral agents in the treatment of HIV-1 infection in adults [see Dosage and Administration (2.1)].

Pediatric Patients:

TYBOST is a CYP3A inhibitor indicated to increase systemic exposure of atazanavir or darunavir (once daily dosing regimen) in combination with other antiretroviral agents in the treatment of HIV-1 infection in pediatric patients weighing at least 14 kg [see Dosage and Administration (2.2), and Drug Interactions (7.3)].

1.2 Limitations of Use

- TYBOST is not interchangeable with ritonavir to increase systemic exposure of darunavir 600 mg twice daily, fosamprenavir, saquinavir, or tipranavir due to lack of exposure data. The use of TYBOST is not recommended with darunavir 600 mg twice daily, fosamprenavir, saquinavir, or tipranavir [see Warnings and Precautions (5.4)].
- Complex or unknown mechanisms of drug interactions preclude extrapolation of ritonavir drug interactions to certain TYBOST interactions. TYBOST and ritonavir when administered with either atazanavir or darunavir may result in different drug interactions when used with concomitant medications [see Warnings and Precautions (5.3), Drug Interactions (7), and Clinical Pharmacology (12.3)].

2 DOSAGE AND ADMINISTRATION

2.1 Recommended Dosage in Adults

Administer TYBOST in conjunction with atazanavir or darunavir and other antiretroviral agents in the treatment of adults with HIV-1 infection. The recommended dosages of TYBOST and atazanavir or darunavir given with food are presented in Table 1. TYBOST must be coadministered at the same time as atazanavir or darunavir [see Drug Interactions (7)]. Consult the prescribing information for atazanavir or darunavir.

Table 1 Recommended Dosing Regimens in Treatment-Naïve or Treatment-Experienced Adults
Patient Populations | Coadministered Agent Dosage | TYBOST Dosage
Treatment-naïve or treatment-experienced | atazanavir 300 mg orally once daily | 150 mg orally once daily
Treatment-naïve or treatment-experienced with no darunavir resistance-associated substitutions | darunavir 800 mg orally once daily | 150 mg orally once daily

2.2 Recommended Dosage in Pediatric Patients

Administer TYBOST in conjunction with atazanavir or darunavir and other antiretroviral agents in the treatment of pediatric patients with HIV-1 infection. The recommended dosages of TYBOST and atazanavir or darunavir given with food are based on weight and presented in Table 2 and Table 3, respectively. TYBOST must be coadministered at the same time as atazanavir or darunavir [see Drug Interactions (7)]. Consult the prescribing information for atazanavir or darunavir.

Table 2 Recommended Dosing Regimen in Treatment-Naïve or Treatment-Experienced Pediatric Patients in Combination with Atazanavir
Body Weight | Atazanavir Dosage | TYBOST Dosage
Weighing at least 14 kg to less than 25 kg | 200 mg orally once daily | 90 mg orally once daily
Weighing at least 25 kg to less than 35 kg | 200 mg orally once daily | 150 mg orally once daily
Weighing at least 35 kg | 300 mg orally once daily | 150 mg orally once daily

Table 3 Recommended Dosing Regimen in Treatment-Naïve or Treatment-Experienced Pediatric Patients with no Darunavir Resistance-Associated Substitutions in Combination with Darunavir
Body Weight | Darunavir Dosage | TYBOST Dosage
Weighing at least 15 kg to less than 25 kg | 600 mg orally once daily | 90 mg orally once daily
Weighing at least 25 kg to less than 30 kg | 600 mg orally once daily | 150 mg orally once daily
Weighing at least 30 kg to less than 40 kg | 675 mg orally once daily | 150 mg orally once daily
Weighing at least 40 kg | 800 mg orally once daily | 150 mg orally once daily

2.3 Testing Prior to Initiation of TYBOST

Prior to or when initiating TYBOST and during treatment with TYBOST, on a clinically appropriate schedule, assess estimated creatinine clearance because TYBOST decreases estimated creatinine clearance due to inhibition of tubular secretion of creatinine without affecting actual renal glomerular function [see Warnings and Precautions (5.1)]. When coadministering TYBOST with TDF, assess estimated creatinine clearance, urine glucose, and urine protein at baseline. In patients with chronic kidney disease, also assess serum phosphorus [see Warnings and Precautions (5.2)].

2.4 Renal Impairment

TYBOST coadministered with TDF is not recommended in patients who have an estimated creatinine clearance below 70 mL/min because dose adjustment of TDF is required below 50 mL/min and such dose adjustments have not been established for coadministration with TYBOST [see Warnings and Precautions (5.2) and Adverse Reactions (6.1)].

2.5 Not Recommended During Pregnancy

TYBOST coadministered with darunavir is not recommended for use during pregnancy because of substantially lower exposures of darunavir and cobicistat during the second and third trimesters [see Use in Specific Populations (8.1) and Clinical Pharmacology (12.3)].

TYBOST coadministered with atazanavir is not recommended for use during pregnancy because of substantially lower exposures of cobicistat during the second and third trimesters [see Use in Specific Populations (8.1) and Clinical Pharmacology (12.3)].

TYBOST coadministered with darunavir or atazanavir should not be initiated in pregnant individuals. An alternative regimen is recommended for individuals who become pregnant during therapy with TYBOST coadministered with darunavir or atazanavir.

3 DOSAGE FORMS AND STRENGTHS

TYBOST, 150 mg: Orange, round, biconvex, film-coated tablets debossed with "GSI" on one side and plain faced on the other side of the tablet.

TYBOST, 90 mg: White, round, biconvex, film-coated tablets debossed with "TYB" on one side and "90" on the other side of the tablet.

4 CONTRAINDICATIONS

The concomitant use of TYBOST with atazanavir or darunavir and the following drugs is contraindicated due to the potential for serious and/or life-threatening events or loss of therapeutic effect [see Drug Interactions (7.3) and Clinical Pharmacology (12.3)].

- Alpha 1-adrenoreceptor antagonist: alfuzosin
- Antianginal: ranolazine
- Antiarrhythmic: dronedarone
- Anticonvulsants: carbamazepine, phenobarbital, phenytoin
- Anti-gout: colchicine
- Antimycobacterial: rifampin
- Antineoplastics: irinotecan [These contraindications apply only to TYBOST coadministered with atazanavir]
- Antipsychotics: lurasidone, pimozide
- Ergot Derivatives: dihydroergotamine, ergotamine, methylergonovine
- Herbal Products: St. John's wort (Hypericum perforatum)
- Hormonal Contraceptives: drospirenone/ ethinyl estradiol
- Lipid-modifying Agents: lomitapide, lovastatin, simvastatin
- Non-nucleoside Reverse Transcriptase Inhibitor: nevirapine
- Phosphodiesterase-5 (PDE-5) Inhibitor: sildenafil when administered as Revatio® for the treatment of pulmonary arterial hypertension
- Protease Inhibitor: indinavir
- Sedative/hypnotics triazolam, orally administered midazolam

5 WARNINGS AND PRECAUTIONS

5.1 Effects on Serum Creatinine

TYBOST decreases estimated creatinine clearance due to inhibition of tubular secretion of creatinine without affecting actual renal glomerular function. This effect should be considered when interpreting changes in estimated creatinine clearance in patients initiating TYBOST, particularly in patients with medical conditions or receiving drugs needing monitoring with estimated creatinine clearance.

Prior to initiating therapy with TYBOST, assess estimated creatinine clearance [see Dosage and Administration (2.3)]. Dosage recommendations are not available for drugs that require dosage adjustments in TYBOST-treated patients with renal impairment [see Adverse Reactions (6.1), Drug Interactions (7.3), and Clinical Pharmacology (12.2)]. Consider alternative medications that do not require dosage adjustments in patients with renal impairment.

Although TYBOST may cause modest increases in serum creatinine and modest declines in estimated creatinine clearance without affecting renal glomerular function, patients who experience a confirmed increase in serum creatinine of greater than 0.4 mg/dL from baseline should be closely monitored for renal safety.

5.2 New Onset or Worsening Renal Impairment When Used with Tenofovir Disoproxil Fumarate

Renal impairment, including cases of acute renal failure and Fanconi syndrome, has been reported when TYBOST was used in an antiretroviral regimen that contained TDF.

- Coadministration of TYBOST and TDF is not recommended in patients who have an estimated creatinine clearance below 70 mL/min because dose adjustment of TDF is required below 50 mL/min and such dose adjustments have not been established for coadministration with TYBOST [see Dosage and Administration (2.3, 2.4)].
- Document urine glucose and urine protein at baseline [see Dosage and Administration (2.3)] and perform routine monitoring of estimated creatinine clearance, urine glucose, and urine protein during treatment when TYBOST is used with TDF. Measure serum phosphorus in patients with or at risk for renal impairment when used with TDF.
- Coadministration of TYBOST and TDF in combination with concomitant or recent use of a nephrotoxic agent is not recommended.

In a clinical trial of TYBOST over 144 weeks (N=692), 10 (2.9%) participants treated with TYBOST coadministered with atazanavir and TRUVADA® and 11 (3.2%) participants treated with ritonavir coadministered with atazanavir and TRUVADA discontinued study drug due to a renal adverse event. Seven of the 10 participants (2.0% overall) in the TYBOST group had laboratory findings consistent with proximal renal tubulopathy leading to study drug discontinuation compared to 7 of 11 participants (2.0% overall) in the ritonavir group. One participant in the TYBOST group had renal impairment at baseline (i.e., estimated creatinine clearance less than 70 mL/min). The laboratory findings in these 7 participants with evidence of proximal tubulopathy improved but did not completely resolve in all participants upon discontinuation of TYBOST coadministered with atazanavir and TRUVADA. Renal replacement therapy was not required in any participant.

5.3 Risk of Serious Adverse Reactions or Loss of Virologic Response Due to Drug Interactions

Initiation of TYBOST, a CYP3A inhibitor, in patients receiving medications metabolized by CYP3A, or initiation of medications metabolized by CYP3A in patients already receiving TYBOST, may increase plasma concentrations of medications metabolized by CYP3A and reduce plasma concentrations of active metabolite(s) formed by CYP3A. Initiation of medications that inhibit or induce CYP3A may respectively increase or decrease concentrations of TYBOST with atazanavir or darunavir.

These interactions may lead to:

- clinically significant adverse reactions, potentially leading to severe, life-threatening, or fatal events from higher exposures of concomitant medications.
- clinically significant adverse reactions from higher exposures of TYBOST and atazanavir or darunavir.

These interactions may lead to:

- loss of therapeutic effect of TYBOST with atazanavir or darunavir and possible development of resistance.
- loss of therapeutic effect of the concomitant medications from lower exposures of active metabolite(s).

See Table 7 for steps to prevent or manage these possible and known significant drug interactions, including dosing recommendations [see Drug Interactions (7)]. Consider the potential for drug interactions prior to and during TYBOST with atazanavir or darunavir therapy; review concomitant medications during TYBOST with atazanavir or darunavir therapy; and monitor for the adverse reactions associated with concomitant medications [see Contraindications (4) and Drug Interactions (7)].

TYBOST or ritonavir when administered with either atazanavir or darunavir may result in different drug interactions when used with concomitant medications. Complex or unknown mechanisms of drug interactions preclude extrapolation of ritonavir drug interactions to certain TYBOST interactions [see Drug Interactions (7) and Clinical Pharmacology (12.3)].

5.4 Antiretrovirals that are Not Recommended in Combination with TYBOST

The following antiretrovirals are not recommended in combination with TYBOST because dosing recommendations for such combinations have not been established and coadministration may result in decreased plasma concentrations of the antiretroviral agents, leading to loss of therapeutic effect and development of resistance:

- More than one antiretroviral that requires pharmacokinetic enhancement (i.e., two protease inhibitors or a protease inhibitor in combination with elvitegravir)
- Darunavir in combination with efavirenz, nevirapine, or etravirine
- Atazanavir in combination with etravirine
- Atazanavir in combination with efavirenz in treatment-experienced patients
- Darunavir 600 mg twice daily
- Other HIV-1 protease inhibitors including fosamprenavir, saquinavir, or tipranavir

TYBOST in combination with fixed-dose combination tablets that contain cobicistat is not recommended.

TYBOST in combination with lopinavir/ritonavir or regimens containing ritonavir is not recommended due to similar effects of TYBOST and ritonavir on CYP3A.

6 ADVERSE REACTIONS

The following adverse reaction is described in greater detail in another section of the labeling:

- New Onset or Worsening Renal Impairment When Used with Tenofovir Disoproxil Fumarate [see Warnings and Precautions (5.2)].

6.1 Clinical Trials Experience

Because clinical trials are conducted under widely varying conditions, adverse reaction rates observed in the clinical trials of a drug cannot be directly compared to rates in the clinical trials of another drug and may not reflect the rates observed in practice.

Adverse Reactions from Clinical Trials Experience in Adults

The safety of TYBOST is based on Week 144 data from a Phase 3 trial, Trial 114, in which 692 antiretroviral treatment-naïve participants with HIV-1 received:

- TYBOST coadministered with atazanavir and TDF/emtricitabine (administered as TRUVADA) (N=344) or
- ritonavir coadministered with atazanavir and TDF/emtricitabine (administered as TRUVADA) (N=348).

The most common adverse reactions (Grades 2−4) and reported in >5% of participants in the TYBOST group were jaundice (6%) and rash (5%). The proportion of participants who discontinued study treatment due to adverse events, regardless of severity, was 11% in both the TYBOST and ritonavir groups. Table 4 displays the frequency of adverse reactions (Grades 2−4) occurring in at least 2% of participants in the TYBOST group in Trial 114.

Table 4 Selected Adverse Reactions [Frequencies of adverse reactions are based on Grades 2–4 adverse events attributed to study drugs.] (Grades 2−4) Reported in ≥2% of Treatment-Naïve Adults with HIV-1 in the TYBOST Coadministered with Atazanavir Group in Trial 114 (Week 144 Analysis)
 | TYBOST Coadministered with Atazanavir + TRUVADA N=344 | Ritonavir Coadministered with Atazanavir + TRUVADA N=348
Jaundice | 6% | 3%
Rash [Rash events include dermatitis allergic, drug hypersensitivity, pruritus generalized, eosinophilic pustular folliculitis, rash, rash generalized, rash macular, rash maculo-papular, rash morbilliform, rash papular, and urticaria.] | 5% | 4%
Ocular icterus | 4% | 2%
Nausea | 2% | 2%
Diarrhea | 2% | 1%
Headache | 2% | 1%

Less Common Adverse Reactions

Selected adverse reactions of at least moderate severity (≥Grade 2) occurring in less than 2% of participants receiving TYBOST coadministered with atazanavir and TRUVADA are listed below. These events have been included because of the investigator’s assessment of potential causal relationship and were considered serious or have been reported in more than one subject treated with TYBOST and with greater frequency compared with ritonavir.

Gastrointestinal Disorders: vomiting, upper abdominal pain

General Disorders and Administration Site Conditions: fatigue

Musculoskeletal and Connective Tissue Disorders: rhabdomyolysis

Psychiatric Disorders: depression, abnormal dreams, insomnia

Renal and Urinary Disorders: nephropathy, Fanconi syndrome acquired, nephrolithiasis

Refer to the prescribing information for atazanavir or darunavir for information regarding adverse reactions with these drugs.

Laboratory Abnormalities: The frequency of laboratory abnormalities (Grades 3−4) occurring in at least 2% of participants in the TYBOST group in Trial 114 is presented in Table 5.

Table 5 Laboratory Abnormalities (Grades 3−4) in ≥2% of Treatment-Naïve Adults with HIV-1 in the TYBOST Coadministered with Atazanavir Group in Trial 114 (Week 144 Analysis)
 | TYBOST + Atazanavir + TRUVADA | Ritonavir + Atazanavir + TRUVADA
Laboratory Parameter Abnormality | N=344 | N=348
Total Bilirubin (>2.5 × ULN) | 73% | 66%
Creatine Kinase (≥10.0 × ULN) | 8% | 9%
Urine RBC (Hematuria) (>75 RBC/HPF) | 6% | 3%
ALT (>5.0 × ULN) | 6% | 3%
AST (>5.0 × ULN) | 4% | 3%
GGT (>5.0 × ULN) | 4% | 2%
Serum Amylase [For participants with serum amylase >1.5 × upper limit of normal, lipase test was also performed. The frequency of increased lipase (Grades 3−4) occurring in the TYBOST (N=46) and ritonavir (N=35) groups was 7% and 3%, respectively.] (>2.0 × ULN) | 4% | 2%
Urine Glucose (Glycosuria) (≥1000 mg/dL) | 3% | 3%
Neutrophils (<750/mm^3) | 3% | 2%
Serum Glucose (Hyperglycemia) (>250 mg/dL) | 2% | 2%

Increase in Serum Creatinine: TYBOST causes increases in serum creatinine and decreases in estimated creatinine clearance due to inhibition of tubular secretion of creatinine without affecting actual renal glomerular function [see Warnings and Precautions (5.1) and Clinical Pharmacology (12.2)]. In Trial 114, increases in serum creatinine and decreases in estimated creatinine clearance occurred early in treatment with TYBOST, after which they stabilized. The mean (± SD) change in estimated glomerular filtration rate (eGFR) by Cockcroft-Gault method after 144 weeks of treatment was –15.1 ± 16.5 mL/min in the TYBOST group and –8.0 ± 16.8 mL/min in the ritonavir group.

Serum Lipids: Changes from baseline in total cholesterol, HDL-cholesterol, LDL-cholesterol, and triglycerides are presented in Table 6. In both groups, mean values for serum lipids remained within the study reference range for each laboratory test. The clinical significance of these changes is unknown.

Table 6 Lipid Values, Mean Change from Baseline, Reported in Treatment-Naïve Adults with HIV-1 Receiving TYBOST Coadministered with Atazanavir + TRUVADA or Ritonavir Coadministered with Atazanavir + TRUVADA in Trial 114 (Week 144 Analysis)
 | TYBOST + Atazanavir + TRUVADA |  | Ritonavir + Atazanavir + TRUVADA
 | Baseline | Week 144 | Baseline | Week 144
 | mg/dL | Change from baseline [The change from baseline is the mean of within-patient changes from baseline for patients with both baseline and Week 144 values. Analysis excludes participants receiving an HMG-CoA reductase inhibitor drug.] | mg/dL | Change from baseline
Total Cholesterol (fasted) | 163 [N=219] | +11 [N=219] | 165 [N=227] | +13 [N=227]
HDL-cholesterol (fasted) | 43 [N=218] | +7 [N=218] | 43 [N=228] | +6 [N=228]
LDL-cholesterol (fasted) | 102 [N=218] | +11 [N=218] | 104 [N=228] | +16 [N=228]
Triglycerides (fasted) | 130 [N=219] | +14 [N=219] | 131 [N=227] | +14 [N=227]

Adverse Reactions from Clinical Trials Experience in Pediatric Participants

The safety of TYBOST was evaluated in an open-label clinical trial (Trial 128) of pediatric participants with HIV-1 administered TYBOST-boosted atazanavir or darunavir plus two nucleoside reverse transcriptase inhibitors; this study included 22 virologically-suppressed participants between the ages of 12 to less than 18 years (weighing ≥35 kg) administered atazanavir (N=14) or darunavir (N=7) through Week 48; 9 virologically-suppressed pediatric participants between the ages of 6 to less than 12 years weighing at least 25 kg to less than 40 kg administered darunavir (N=9) through Week 48; and 11 virologically-suppressed participants at least 2 years of age (weighing ≥14 kg to <25 kg) administered darunavir through Week 48 [see Drug Interactions (7.3), Use in Specific Populations (8.4), Clinical Studies (14.2)]. In this trial, the safety profile of TYBOST was similar to that in adults.

7 DRUG INTERACTIONS

7.1 Potential Effect of Cobicistat (Coadministered with Atazanavir or Darunavir) on the Pharmacokinetics of Concomitant Drugs

Cobicistat is an inhibitor of CYP3A and CYP2D6. The transporters that cobicistat inhibits include p-glycoprotein (P-gp), BCRP, OATP1B1, and OATP1B3. The plasma concentration of drugs that are primarily metabolized by CYP3A or CYP2D6, or are substrates of P-gp, BCRP, OATP1B1, or OATP1B3 may be increased if those drugs are coadministered with TYBOST.

Based on in vitro data, cobicistat is not expected to induce CYP1A2 or CYP2B6 and based on in vivo data, cobicistat is not expected to induce MDR1 or, in general, CYP3A to a clinically significant extent. The induction effect of cobicistat on CYP2C9, CYP2C19, or UGT1A1 is unknown, but is expected to be low based on CYP3A in vitro induction data.

Coadministration of TYBOST with atazanavir or darunavir with drugs highly dependent on CYP3A for clearance and for which elevated plasma concentrations are associated with serious and/or life-threatening events is contraindicated. Coadministration with drugs that have active metabolite(s) formed by CYP3A may result in reduced plasma concentrations of these active metabolite(s). Coadministration with other CYP3A substrates may require a dose adjustment or additional monitoring as shown in Table 7.

7.2 Potential Effect of Concomitant Drugs on the Pharmacokinetics of Cobicistat (Coadministered with Atazanavir or Darunavir)

Cobicistat is metabolized by CYP3A, and to a minor extent, by CYP2D6. Atazanavir and darunavir are also metabolized by CYP3A.

Coadministration of TYBOST with atazanavir or darunavir in combination with drugs that induce CYP3A activity have the potential to decrease plasma concentrations of cobicistat, atazanavir, and darunavir, which may lead to loss of therapeutic effect and development of resistance (see Table 7).

Coadministration of TYBOST with atazanavir or darunavir in combination with other drugs that inhibit CYP3A may further increase the plasma concentrations of cobicistat, atazanavir, and darunavir (see Table 7).

7.3 Established and Other Potentially Significant Interactions

Coadministration of TYBOST with fosamprenavir, saquinavir, or tipranavir is not recommended because pharmacokinetic data are not available to provide appropriate dosing recommendations. Use of TYBOST with lopinavir is not recommended because lopinavir is co-formulated with ritonavir.

Table 7 provides dosing recommendations as a result of drug interactions with TYBOST coadministered with atazanavir or darunavir. These recommendations are based on either drug interaction trials or predicted interactions due to the expected magnitude of the interaction and potential for serious adverse events or loss of therapeutic effect [see Contraindications (4), Warnings and Precautions (5.3, 5.4), and Clinical Pharmacology (12.3)].

In Table 7, if not specifically stated, the drug interaction information applies to both coadministered agents: TYBOST coadministered with atazanavir or darunavir [see Clinical Pharmacology (12.3)].

In addition to the drug interactions noted in Table 7, TYBOST is not recommended for use in combination with fixed-dose combination tablets that contain cobicistat, lopinavir/ritonavir or regimens containing ritonavir, or in combination with more than one antiretroviral agent that requires pharmacokinetic enhancement [see Warnings and Precautions (5.4)].

Evaluate whether dosing adjustments of concomitant medications or coadministered antiretroviral drugs are necessary in:

- Patients on a stable concomitant medication who initiate or switch to a TYBOST-containing regimen
- Patients on a TYBOST-containing regimen who initiate a new concomitant medication
- Patients initiating a TYBOST-containing regimen and a new concomitant medication simultaneously

Under these circumstances, also monitor for adverse events and/or monitor concentrations of concomitant medications if appropriate.

No dose adjustment is required when TDF or rilpivirine are coadministered with TYBOST and atazanavir or darunavir.

Table 7 Established and Other Potentially Significant [This table is not all inclusive.] Drug Interactions: Alteration in Dose or Regimen May Be Recommended Based on Drug Interaction Studies or Predicted Interaction
Concomitant Drug Class: Drug Name | Potential Effect [↑ = Increase, ↓ = Decrease, ↔ = No change] | Clinical Comment
Antiretroviral Agents: Nucleotide Reverse Transcriptase Inhibitor (NRTI)
tenofovir alafenamide | ↔tenofovir alafenamide ↑tenofovir alafenamide | TYBOST coadministered with darunavir in pediatric patients weighing at least 15 kg: No dose adjustment. TYBOST coadministered with atazanavir in pediatric patients weighing 14 to less than 35 kg: Coadministration is not recommended [see Use in Specific Populations (8.4)].
Antiretroviral Agents: Non-Nucleoside Reverse Transcriptase Inhibitors (NNRTIs)
efavirenz | ↓ cobicistat ↓ darunavir ↓ atazanavir | TYBOST coadministered with darunavir: Coadministration of darunavir and TYBOST with efavirenz is not recommended because it may result in the loss of therapeutic effect and development of resistance to darunavir. TYBOST coadministered with atazanavir: In treatment-naïve adult patients: Atazanavir 400 mg with TYBOST 150 mg should be coadministered once daily as a single dose with food, and efavirenz 600 mg should be administered once daily on an empty stomach, preferably at bedtime. In treatment-experienced adult patients: Coadministration of atazanavir and TYBOST with efavirenz in treatment-experienced patients is not recommended because it may result in the loss of therapeutic effect and development of resistance to atazanavir.
etravirine | ↓ cobicistat darunavir: effect unknown ↓ atazanavir | Coadministration with etravirine is not recommended because it may result in the loss of therapeutic effect and development of resistance to atazanavir or darunavir.
nevirapine | ↓ atazanavir ↑ nevirapine ↓ cobicistat darunavir: effect unknown | Contraindicated with TYBOST coadministered with atazanavir only: Coadministration of atazanavir with nevirapine is contraindicated due to potential for loss of atazanavir therapeutic effect and development of resistance, and potential for nevirapine-associated adverse reactions. TYBOST coadministered with darunavir: TYBOST coadministration with nevirapine and darunavir is not recommended because it may result in the loss of therapeutic effect and development of resistance to darunavir.
Antiretroviral Agents: CCR5 Antagonists
maraviroc | ↑ maraviroc | Maraviroc is a substrate of CYP3A. When coadministering with maraviroc, adult patients should receive maraviroc 150 mg twice daily.
Antiretroviral Agents: Protease Inhibitors
indinavir |  | Contraindicated with TYBOST coadministered with atazanavir only: Both atazanavir and indinavir are associated with indirect (unconjugated) hyperbilirubinemia.
Other Agents:
Alpha 1- adrenoreceptor antagonist: alfuzosin | ↑ alfuzosin | Coadministration with alfuzosin is contraindicated due to potential for serious and/or life-threatening reactions such as hypotension.
Antianginal ranolazine | ↑ ranolazine | Coadministration with ranolazine is contraindicated due to potential for serious and/or life-threatening reactions.
Antacids: e.g., aluminum and magnesium hydroxide (please also see H2-Receptor Antagonists and Proton Pump Inhibitors below) | ↓ atazanavir | TYBOST coadministered with atazanavir: With concomitant use, administer a minimum of 2 hours apart.
Antiarrhythmics: dronedarone | ↑ dronedarone | Coadministration with dronedarone is contraindicated due to potential for serious and/or life-threatening reactions such as cardiac arrhythmias.
digoxin | ↑ digoxin | When coadministering with digoxin, titrate the digoxin dose and monitor digoxin concentrations.
Other antiarrhythmics: e.g., amiodarone disopyramide flecainide mexiletine propafenone quinidine | ↑ antiarrhythmics | Clinical monitoring is recommended upon coadministration with antiarrhythmics.
Antibacterials (macrolide or ketolide antibiotics): clarithromycin erythromycin telithromycin | ↑ clarithromycin ↑ erythromycin ↑ telithromycin ↑ cobicistat ↑ atazanavir ↑ darunavir | Consider alternative antibiotics with concomitant use of TYBOST coadministered with atazanavir or darunavir.
Anticancer Agents: irinotecan | ↑ irinotecan | Contraindicated with TYBOST coadministered with atazanavir only: Coadministration of atazanavir with irinotecan is contraindicated due to potential for increased irinotecan toxicity.
dasatinib nilotinib vinblastine vincristine | ↑ anticancer agents | A decrease in the dosage or an adjustment of the dosing interval of dasatinib or nilotinib may be necessary upon coadministration with TYBOST coadministered with atazanavir or darunavir. Consult the dasatinib and nilotinib prescribing information for dosing instructions. For vincristine and vinblastine, monitor for hematologic or gastrointestinal side effects.
Anticoagulants: Direct Oral Anticoagulants (DOACs) apixaban rivaroxaban betrixaban dabigatran edoxaban | ↑ apixaban | TYBOST coadministered with atazanavir or darunavir: Due to potentially increased bleeding risk, dosing recommendations for coadministration of apixaban with TYBOST depends on the apixaban dose. Refer to apixaban dosing instructions for coadministration with strong CYP3A and P-gp inhibitors in apixaban prescribing information.
 | ↑ rivaroxaban | Coadministration of rivaroxaban with TYBOST is not recommended because it may lead to an increased bleeding risk.
 | atazanavir: ↑ betrixaban ↑ dabigatran ↑ edoxaban | TYBOST coadministered with atazanavir: Due to potentially increased bleeding risk, dosing recommendations for coadministration of betrixaban, dabigatran, or edoxaban with a P-gp inhibitor such as TYBOST coadministered with atazanavir depends on DOAC indication and renal function. Refer to DOAC dosing instructions for coadministration with P-gp inhibitors in DOAC prescribing information.
 | darunavir: ↔ betrixaban ↔ dabigatran ↔ edoxaban | TYBOST coadministered with darunavir: No dose adjustment.
warfarin | warfarin: effect unknown | Monitor the international normalized ratio (INR) upon coadministration of TYBOST with warfarin.
Anticonvulsants: carbamazepine, phenobarbital, phenytoin | ↓ atazanavir ↓ darunavir ↓ cobicistat | Coadministration with carbamazepine, phenobarbital, or phenytoin is contraindicated due to potential for loss of therapeutic effect and development of resistance.
Anticonvulsants with CYP3A induction effects that are NOT contraindicated e.g., eslicarbazepine, oxcarbazepine | ↓ cobicistat ↓ atazanavir darunavir: effect unknown | Consider alternative anticonvulsant or antiretroviral therapy to avoid potential changes in exposures. If coadministration is necessary, monitor for lack or loss of virologic response.
Anticonvulsants that are metabolized by CYP3A e.g., clonazepam | ↑ clonazepam | Clinical monitoring of anticonvulsants is recommended.
Antidepressants: Selective Serotonin Reuptake Inhibitors (SSRIs) e.g., paroxetine Tricyclic Antidepressants (TCAs) e.g., amitriptyline desipramine imipramine nortriptyline Other antidepressants: trazodone | SSRIs: effects unknown ↑ TCAs ↑ trazodone | When coadministering with SSRIs, TCAs, or trazodone, careful dose titration of the antidepressant to the desired effect, including using the lowest feasible initial or maintenance dose, and monitoring for antidepressant response are recommended.
Antifungals: itraconazole ketoconazole | ↑ itraconazole ↑ ketoconazole | Specific dosing recommendations are not available for coadministration with itraconazole or ketoconazole.
voriconazole | Voriconazole: effects unknown ↑ cobicistat ↑ atazanavir ↑ darunavir | Coadministration with voriconazole is not recommended unless the benefit/risk assessment justifies the use of voriconazole.
Anti-gout: colchicine | ↑ colchicine | Coadministration with colchicine is contraindicated in patients with renal and/or hepatic impairment due to potential for serious and/or life-threatening reactions. Treatment of gout flares in adult patients – coadministration of colchicine: 0.6 mg (1 tablet) x 1 dose, followed by 0.3 mg (half tablet) 1 hour later. Treatment course to be repeated no earlier than 3 days. Prophylaxis of gout flares in adult patients – coadministration of colchicine: If the original regimen was 0.6 mg twice a day, the regimen should be adjusted to 0.3 mg once a day. If the original regimen was 0.6 mg once a day, the regimen should be adjusted to 0.3 mg once every other day. Treatment of familial Mediterranean fever in adult patients – coadministration of colchicine: Maximum daily dose of 0.6 mg (may be given as 0.3 mg twice a day).
Antimycobacterial: rifampin | ↓ atazanavir ↓ darunavir ↓ cobicistat | Coadministration with rifampin is contraindicated due to potential for loss of therapeutic effect and development of resistance.
rifabutin | ↑ rifabutin cobicistat: effects unknown darunavir: effects unknown atazanavir: effects unknown | The recommended adult dosage regimen for rifabutin is 150 mg every other day. Monitor for rifabutin associated adverse reactions including neutropenia and uveitis.
Antiplatelets:
ticagrelor | ↑ ticagrelor | Coadministration with ticagrelor is not recommended.
clopidogrel | ↓ clopidogrel active metabolite | Coadministration with clopidogrel is not recommended due to potential reduction of the antiplatelet activity of clopidogrel.
prasugrel | ↔ prasugrel active metabolite | No dose adjustment is needed when prasugrel is co-administered with TYBOST.
Antipsychotics:
lurasidone | ↑ lurasidone | Coadministration with lurasidone is contraindicated due to potential for serious and/or life-threatening reactions.
pimozide | ↑ pimozide | Coadministration with pimozide is contraindicated due to potential for serious and/or life-threatening reactions such as cardiac arrhythmias.
quetiapine | ↑ quetiapine | Initiation of TYBOST coadministered with atazanavir or darunavir in patients taking quetiapine: Consider alternative antiretroviral therapy to avoid increases in quetiapine exposure. If coadministration is necessary, reduce the quetiapine dose to 1/6 of the current dose and monitor for quetiapine-associated adverse reactions. Refer to the quetiapine prescribing information for recommendations on adverse reaction monitoring. Initiation of quetiapine in patients taking TYBOST coadministered with atazanavir or darunavir: Refer to the quetiapine prescribing information for initial dosing and titration of quetiapine.
Other antipsychotics: e.g., perphenazine risperidone thioridazine | ↑ antipsychotic | A decrease in the dose of antipsychotics that are metabolized by CYP3A or CYP2D6 may be needed upon coadministration.
Beta-Blockers: e.g., metoprolol carvedilol timolol | ↑ beta-blockers | Clinical monitoring is recommended for coadministration with beta-blockers that are metabolized by CYP2D6.
Calcium Channel Blockers: e.g., amlodipine diltiazem felodipine nifedipine verapamil | ↑ calcium channel blockers | Clinical monitoring is recommended for coadministration with calcium channel blockers metabolized by CYP3A.
Corticosteroids: e.g., betamethasone budesonide ciclesonide dexamethasone fluticasone methylprednisolone mometasone triamcinolone | ↓ cobicistat ↓ atazanavir ↓ darunavir ↑ corticosteroids | Coadministration with oral dexamethasone or other systemic corticosteroids that induce CYP3A may result in loss of therapeutic effect and development of resistance to atazanavir or darunavir. Consider alternative corticosteroids. Coadministration with corticosteroids (all routes of administration) whose exposures are significantly increased by strong CYP3A inhibitors can increase the risk for Cushing’s syndrome and adrenal suppression. Alternative corticosteroids including beclomethasone, prednisone, and prednisolone (whose PK and/or PD are less affected by strong CYP3A inhibitors relative to other studied steroids) should be considered, particularly for long-term use.
Endothelin Receptor Antagonists: bosentan | ↑ bosentan ↓ cobicistat ↓ darunavir ↓ atazanavir | Initiation of bosentan in adult patients taking TYBOST coadministered with atazanavir or darunavir: In patients who have been receiving TYBOST coadministered with atazanavir or darunavir for at least 10 days, start bosentan at 62.5 mg once daily or every other day based upon individual tolerability. Initiation of TYBOST coadministered with atazanavir or darunavir in adult patients taking bosentan: Discontinue use of bosentan at least 36 hours prior to initiation of TYBOST coadministered with atazanavir or darunavir. After at least 10 days following the initiation of TYBOST combined with atazanavir or darunavir, resume bosentan at 62.5 mg once daily or every other day based upon individual tolerability. Switching from ritonavir to TYBOST coadministered with atazanavir or darunavir: Maintain bosentan dose.
Ergot Derivatives: dihydroergotamine, ergotamine, methylergonovine | ↑ ergot derivatives | Coadministration is contraindicated due to potential for serious and/or life-threatening reactions such as acute ergot toxicity characterized by peripheral vasospasm and ischemia of the extremities and other tissues.
H2-Receptor Antagonists: e.g., famotidine | ↓ atazanavir | TYBOST coadministered with atazanavir in adult patients: Administer atazanavir/TYBOST either at the same time or a minimum of 10 hours after administering H2-receptor antagonists. The dose of the H2-receptor antagonist should not exceed a dose comparable to famotidine 40 mg twice daily in treatment-naïve adult patients or 20 mg twice daily in treatment-experienced adult patients. TYBOST coadministered with atazanavir and TDF in adult patients: Treatment-experienced adult patients: The recommended once daily dosage regimen is TYBOST 150 mg coadministered with atazanavir 400 mg with concomitant use of H2-receptor antagonists and tenofovir DF.
Herbal Products: St. John’s wort (Hypericum perforatum) | ↓ atazanavir ↓ darunavir ↓ cobicistat | Coadministration is contraindicated due to potential for loss of therapeutic effect and development of resistance.
Hormonal Contraceptives: |  | Additional or alternative non-hormonal forms of contraception should be considered when estrogen based contraceptives are coadministered with TYBOST and atazanavir or darunavir.
drospirenone/ethinyl estradiol | atazanavir: ↑ drospirenone | Contraindicated with TYBOST coadministered with atazanavir only: Coadministration of atazanavir with drospirenone is contraindicated due to potential for drospirenone-associated hyperkalemia.
 | darunavir: ↑ drospirenone ↓ ethinyl estradiol | TYBOST coadministered with darunavir: For coadministration with drospirenone, clinical monitoring is recommended due to the potential for hyperkalemia.
Other progestin/estrogen contraceptives | progestin: effects unknown estrogen: effects unknown | No data are available to make recommendations on the coadministration of TYBOST and atazanavir or darunavir with other hormonal contraceptives.
Immuno-suppressants: cyclosporine everolimus sirolimus tacrolimus | ↑ immuno-suppressants | These immunosuppressant agents are metabolized by CYP3A. Therapeutic drug monitoring is recommended if coadministered.
Inhaled Beta Agonist: salmeterol | ↑ salmeterol | Coadministration with salmeterol is not recommended and may result in increased risk of cardiovascular adverse events associated with salmeterol, including QT prolongation, palpitations, and sinus tachycardia.
Lipid-modifying Agents: HMG-CoA reductase inhibitors: lovastatin simvastatin | ↑ lovastatin ↑ simvastatin | Coadministration with lovastatin or simvastatin is contraindicated due to potential for serious reactions such as myopathy including rhabdomyolysis.
Other HMG-CoA reductase inhibitors: e.g., atorvastatin rosuvastatin | ↑ HMG-CoA reductase inhibitors | Coadministration of atazanavir and TYBOST with atorvastatin is not recommended. For HMG-CoA reductase inhibitors that are not contraindicated with TYBOST coadministered with atazanavir or darunavir, start with the lowest recommended dose and titrate while monitoring for safety (e.g., myopathy). Dosage recommendations with atorvastatin or rosuvastatin are as follows. TYBOST coadministered with atazanavir in adult patients:; - Rosuvastatin dosage should not exceed 10 mg; TYBOST coadministered with darunavir in adult patients:; - Atorvastatin dosage should not exceed 20 mg - Rosuvastatin dosage should not exceed 20 mg
Other lipid-modifying agents: lomitapide | ↑ lomitapide | Coadministration with lomitapide is contraindicated due to potential for markedly increased transaminases.
Narcotic Analgesics For treatment of opioid dependence: buprenorphine buprenorphine/ naloxone methadone | buprenorphine or buprenorphine/ naloxone: effects unknown methadone: effects unknown | Initiation of buprenorphine, buprenorphine/naloxone, or methadone in patients taking TYBOST coadministered with atazanavir or darunavir: Carefully titrate the dose of buprenorphine, buprenorphine/naloxone, or methadone to the desired effect; use the lowest feasible initial or maintenance dose. Initiation of TYBOST coadministered with atazanavir or darunavir in patients taking buprenorphine, buprenorphine/naloxone, or methadone: A dose adjustment for buprenorphine, buprenorphine/naloxone, or methadone may be needed. Monitor clinical signs and symptoms.
fentanyl | ↑ fentanyl | Careful monitoring of therapeutic and adverse effects of fentanyl (including potentially fatal respiratory depression) is recommended with coadministration.
tramadol | ↑ tramadol | A dose decrease may be needed for tramadol with concomitant use.
Phosphodiesterase-5 (PDE-5) Inhibitors: avanafil sildenafil tadalafil vardenafil | ↑ PDE-5 inhibitors | Coadministration with avanafil is not recommended because a safe and effective avanafil dosage regimen has not been established. Coadministration with TYBOST coadministered with atazanavir or darunavir may result in an increase in PDE-5 inhibitor associated adverse events, including hypotension, syncope, visual disturbances, and priapism. Use of PDE-5 inhibitors for pulmonary arterial hypertension (PAH):; - Use of sildenafil is contraindicated when used for the treatment of PAH due to potential for sildenafil-associated adverse reactions (which include visual disturbances, hypotension, priapism, and syncope). - The following dose adjustments are recommended for tadalafil concomitant use: Initiation of tadalafil in adult patients taking TYBOST coadministered with atazanavir or darunavir: In adult patients taking TYBOST coadministered with atazanavir or darunavir for at least 1 week, start tadalafil at 20 mg once daily. Increase tadalafil dose to 40 mg once daily based upon individual tolerability. Initiation of TYBOST coadministered with atazanavir or darunavir in adult patients taking tadalafil: Avoid use of tadalafil during the initiation of TYBOST coadministered with atazanavir or darunavir. Stop tadalafil at least 24 hours prior to starting TYBOST coadministered with atazanavir or darunavir. After at least one week following initiation of TYBOST coadministered with atazanavir or darunavir, resume tadalafil at 20 mg once daily. Increase tadalafil dose to 40 mg once daily based upon individual tolerability. Patients switching from ritonavir to TYBOST coadministered with atazanavir or darunavir: Maintain tadalafil dose.; Use of PDE-5 inhibitors for erectile dysfunction in adult patients: Sildenafil at a single dose not exceeding 25 mg in 48 hours, tadalafil at a single dose not exceeding 10 mg in 72 hours, or vardenafil at a single dose not exceeding 2.5 mg in 72 hours can be used with increased monitoring for PDE-5 inhibitor associated adverse events.
Proton-pump Inhibitors (PPIs) e.g., omeprazole | ↓ atazanavir | TYBOST coadministered with atazanavir in adult patients: In treatment-naïve adult patients, administer TYBOST with atazanavir a minimum of 12 hours after administering PPIs. The dose of the PPI should not exceed a dose comparable to omeprazole 20 mg daily. In treatment-experienced adult patients, coadministration with PPIs, with or without tenofovir, is not recommended.
Sedative/Hypnotics:
midazolam (oral), triazolam | ↑ midazolam ↑ triazolam | Coadministration with triazolam or oral administered midazolam is contraindicated due to potential for serious and/or life-threatening reactions such as prolonged or increased sedation or respiratory depression. Triazolam and orally administered midazolam are extensively metabolized by CYP3A. Coadministration of triazolam or orally administered midazolam with TYBOST may cause large increases in the concentrations of these benzodiazepines.
Other benzodiazepines: e.g., parenterally administered midazolam clorazepate diazepam estazolam flurazepam | ↑ sedatives/hypnotics | Coadministration with parenteral midazolam may increase plasma concentrations of midazolam. Coadministration should be done in a setting that ensures close clinical monitoring and appropriate medical management in case of respiratory depression and/or prolonged sedation. Dosing reduction for midazolam should be considered, especially if more than a single dose of midazolam is administered.
buspirone zolpidem |  | With other sedatives/hypnotics that are CYP3A metabolized, dose reduction may be necessary and clinical monitoring is recommended.

8 USE IN SPECIFIC POPULATIONS

8.1 Pregnancy

Pregnancy Exposure Registry

There is a pregnancy exposure registry that monitors fetal outcomes in individuals exposed to TYBOST during pregnancy. Healthcare providers are encouraged to register patients by calling the Antiretroviral Pregnancy Registry (APR) 1-800-258-4263.

Risk Summary

TYBOST coadministered with darunavir or atazanavir is not recommended during pregnancy [see Dosage and Administration (2.5)]. In a clinical trial of individuals taking cobicistat coadministered with darunavir, exposures of cobicistat and darunavir were substantially lower during the second and third trimesters of pregnancy [see Data and Clinical Pharmacology (12.3)].

TYBOST use during pregnancy has been evaluated in a limited number of individuals as reported by the APR, and available data show no significant difference in the rate of overall birth defects for cobicistat compared with the background rate for major defects of 2.7% in a U.S. reference population of the Metropolitan Atlanta Congenital Defects Program (MACDP) (see Data). The rate of miscarriage is not reported in the APR. The estimated background rate of miscarriage in clinically recognized pregnancies in the U.S. general population is 15−20%.

In animal reproduction studies in rats and rabbits, no evidence of fetal harm was observed with oral administration of cobicistat during organogenesis at doses that produced exposures up to 1.4 and 3.3 times, respectively, the maximal recommended human dose (MRHD) of 150 mg (see Data). Because TYBOST is coadministered with atazanavir or darunavir and other antiretroviral drugs, also refer to the prescribing information of each drug for information about pregnancy.

Data

Human Data

Cobicistat coadministered with darunavir as a fixed dose combination, in combination with a background regimen, was evaluated in a clinical trial of 7 pregnant individuals taking darunavir/cobicistat prior to enrollment and who were willing to remain on darunavir/cobicistat throughout the study. The study period included the second and third trimesters, and through 12 weeks postpartum. Six pregnant individuals completed the trial.

Exposure to darunavir and cobicistat as part of an antiretroviral regimen was substantially lower during the second and third trimesters of pregnancy compared with postpartum [see Clinical Pharmacology (12.3)].

One out of 6 individuals who completed the study experienced virologic failure with HIV-1 RNA >1,000 copies/mL from the third trimester visit through the postpartum period. Five individuals had sustained virologic response (HIV-1 RNA <50 copies/mL) throughout the study period. There are no clinical data on the virologic response when darunavir/cobicistat is initiated during pregnancy.

There were no new clinically relevant safety findings compared with the known safety profile of darunavir/cobicistat in adult participants with HIV-1.

The APR has received prospective reports of live births following exposure to cobicistat-containing regimens during pregnancy, including over 600 exposures in the first trimester and over 90 exposures in the second/third trimester. The prevalence of birth defects in live births was 3.5% (95% CI: 2.2% to 5.3%) and 3.2% (95% CI: 0.7% to 9.1%) following first trimester and second/third trimester exposure, respectively, to cobicistat-containing regimens. Methodological limitations of the APR include the use of MACDP as the external comparator group. The MACDP population is not disease-specific, evaluates women and infants from a limited geographic area, and does not include outcomes for births that occurred at <20 weeks gestation.

Animal Data

Cobicistat was administered orally to pregnant rats at doses of 0, 25, 50, and 125 mg/kg/day on gestation day 6 to 17. Maternal toxicity (adverse clinical signs, decreased body weight and food consumption) was noted at 125 mg/kg/day and was associated with increases in postimplantation loss and decreased fetal weights. No malformations were noted at doses up to 125 mg/kg/day. Systemic exposures (AUC) at 50 mg/kg/day in pregnant females were 1.4-fold higher than the exposures at the MRHD.

In pregnant rabbits, cobicistat was administered orally at doses of 0, 20, 50, and 100 mg/kg/day during the gestation days 7 to 20. No maternal or embryo/fetal effects were noted at the highest dose of 100 mg/kg/day. Systemic exposures (AUC) at 100 mg/kg/day were 3.3-fold higher than exposures at the MRHD.

In a pre- and postnatal developmental study, cobicistat was administered orally at doses of 0, 10, 30, and 75 mg/kg from gestation day 6 to postnatal day 20, 21, or 22. At doses of 75 mg/kg/day of cobicistat, neither maternal nor developmental toxicity was noted. Systemic exposures (AUC) at this dose were slightly lower than (0.9-fold) the MRHD.

8.2 Lactation

Risk Summary

There is no information regarding the presence of cobicistat in human milk, the effects on the breastfed infant, or the effects on milk production. Cobicistat is present in rat milk (see Data).

Potential risks of breastfeeding include: (1) HIV-1 transmission to HIV-1–negative infants; (2) developing viral resistance in HIV-1–positive infants; and (3) adverse reactions in a breastfed infant similar to those seen in adults.

Animal Data

During the prenatal and postnatal development toxicology study at doses up to 75 mg/kg/day, mean cobicistat milk to plasma ratio of up to 1.9 was measured 2 hours after administration to rats on lactation Day 10.

8.3 Females and Males of Reproductive Potential

Contraception

TYBOST interacts with certain oral contraceptives [see Drug Interactions (7.3)].

8.4 Pediatric Use

The safety and effectiveness of TYBOST coadministered with atazanavir or darunavir and two nucleoside reverse transcriptase inhibitors for the treatment of HIV-1 infection have been established in pediatric patients weighing at least 14 kg [see Indications and Usage (1.1) and Dosage and Administration (2.2)].

Use of TYBOST and Darunavir

Adolescent Patients Weighing at Least 40 kg

Use of TYBOST and darunavir for this indication is supported by evidence from adequate and well-controlled studies in adults, and by pharmacokinetic, safety, and virologic data from an open-label trial (Trial 128; cohort 1 [Part A]) in virologically suppressed pediatric participants with HIV-1 aged 12 years and older (n=7). The safety, pharmacokinetics, and effectiveness in these participants were similar to that in adults [see Adverse Reactions (6.1), Clinical Pharmacology (12.3), and Clinical Studies (14.2)].

Pediatric Patients Weighing at Least 15 kg to Less than 40 kg:

Use of TYBOST and darunavir in combination with other ARVs is supported by evidence from adequate and well-controlled studies in adults, and by pharmacokinetic, safety, and efficacy data from an open-label trial (Trial 128; cohorts 2 and 3) in pediatric participants with HIV-1 at least 2 years of age and weighing at least 15 kg to less than 40 kg (n=20, all of whom were virologically suppressed at baseline).

The safety, pharmacokinetics, and effectiveness of TYBOST when administered with darunavir in pediatric patients weighing at least 15 kg to less than 40 kg were similar to that in adults [see Adverse Reactions (6.1), Clinical Pharmacology (12.3), and Clinical Studies (14.2)].

Pediatric Patients Weighing Less than 15 kg:

Safety, pharmacokinetics, and effectiveness of TYBOST in combination with darunavir in pediatric patients weighing less than 15 kg have not been established.

Use of TYBOST and Atazanavir

Adolescent Patients Weighing at Least 35 kg:

Use of TYBOST and atazanavir is supported by evidence from adequate and well-controlled studies in adults, and by safety, pharmacokinetic, and efficacy data from an open-label trial (Trial 128; cohort 1 [Part A]) in pediatric participants with HIV-1 at least 12 years of age (n=14). The safety, pharmacokinetics, and effectiveness in these participants were similar to that in adults [see Adverse Reactions (6.1), Clinical Pharmacology (12.3), and Clinical Studies (14.2)].

Pediatric Patients Weighing at Least 14 kg to Less than 35 kg:

- Use of TYBOST and Atazanavir with Tenofovir Alafenamide (TAF)

The use of TYBOST in combination with atazanavir and TAF in pediatric patients weighing less than 35 kg is not recommended.

The use of TYBOST with atazanavir and emtricitabine/tenofovir alafenamide (FTC/TAF) was studied in pediatric participants weighing at least 14 kg to less than 35 kg. In Trial 128, patients who received ATV +cobicistat in cohort 2 (25 kg to <40 kg, n=14) and cohort 3 (14 kg to <25 kg, n=15) showed TAF exposures (Cmax and AUC) that exceeded adult exposures by 4-5-fold in cohort 2 and 2-3-fold in cohort 3. Limited safety data were available to support the increased TAF exposures. Therefore, the use of TYBOST with atazanavir and TAF is not recommended in pediatric participants weighing at least 14 kg to less than 35 kg [see Drug Interactions (7.3)].
- Use of TYBOST and Atazanavir with other antiretrovirals other than TAF
Use of TYBOST and atazanavir is supported by evidence from adequate and well-controlled studies in adults, and by pharmacokinetic data from Trial 128 in pediatric participants weighing at least 14 kg to less than 35 kg. In this population, the pharmacokinetics of atazanavir and cobicistat were similar to adults [see Clinical Pharmacology (12.3)].

Pediatric Patients Weighing Less than 14 kg:

Safety, pharmacokinetics, and effectiveness of TYBOST in combination with atazanavir in pediatric participants weighing less than 14 kg have not been established.

8.5 Geriatric Use

Clinical trials of TYBOST did not include sufficient numbers of participants aged 65 years and older to determine whether they respond differently from younger participants.

8.6 Renal Impairment

No dosage adjustment of TYBOST is required in patients with renal impairment, including those with severe renal impairment. No clinically relevant differences in cobicistat pharmacokinetics were observed between participants with severe renal impairment and healthy participants. TYBOST is coadministered with atazanavir or darunavir; therefore, refer to the prescribing information for atazanavir or darunavir for information regarding dosing recommendations of these drugs in patients with renal impairment [see Clinical Pharmacology (12.3)].

TYBOST has been shown to decrease estimated creatinine clearance without affecting actual renal glomerular function. Dosing recommendations are not available for drugs that require dosing adjustment for renal impairment when used in combination with TYBOST [see Dosage and Administration (2), Warnings and Precautions (5.1), Adverse Reactions (6.1), and Clinical Pharmacology (12.2)].

8.7 Hepatic Impairment

No dosing adjustment of TYBOST is necessary for patients with mild-to-moderate hepatic impairment. No data are available in patients with severe hepatic impairment. TYBOST is coadministered with atazanavir or darunavir and other antiretroviral drugs; therefore, refer to the prescribing information of these other drugs for information regarding dosing recommendations in patients with hepatic impairment [see Clinical Pharmacology (12.3)].

10 OVERDOSAGE

If overdose occurs, the patient must be monitored for evidence of toxicity. Treatment of overdose with TYBOST consists of general supportive measures including monitoring of vital signs, as well as observation of the clinical status of the patient.

As cobicistat is highly bound to plasma proteins, it is unlikely that it will be significantly removed by hemodialysis or peritoneal dialysis.

11 DESCRIPTION

TYBOST (cobicistat) is a mechanism-based CYP3A inhibitor.

The chemical name for cobicistat is 1,3-thiazol-5-ylmethyl [(2R,5R)-5-{[(2S)-2-[(methyl{[2-(propan-2-yl)-1,3-thiazol-4-yl]methyl}carbamoyl)amino]-4-(morpholin-4-yl)butanoyl]amino}-1,6-diphenylhexan-2-yl]carbamate. It has a molecular formula of C40H53N7O5S2 and a molecular weight of 776.0. It has the following structural formula:

Cobicistat is adsorbed onto silicon dioxide. Cobicistat on silicon dioxide is a white to pale yellow solid with a solubility of 0.1 mg/mL in water at 20 °C.

TYBOST tablets are for oral administration. Each tablet contains 150 mg or 90 mg of cobicistat. The 150 mg and 90 mg tablets include the following inactive ingredients: silicon dioxide, microcrystalline cellulose, croscarmellose sodium, and magnesium stearate. The 150 mg tablets are film-coated with a coating material containing the following inactive ingredients: polyethylene glycol, polyvinyl alcohol, talc, titanium dioxide, sunset yellow FCF (FD&C Yellow #6) aluminum lake, and iron oxide yellow. The 90 mg tablets are film-coated with a coating material containing the following inactive ingredients: polyvinyl alcohol, titanium dioxide, polyethylene glycol, and talc.

12 CLINICAL PHARMACOLOGY

12.1 Mechanism of Action

Cobicistat is a mechanism-based inhibitor of cytochrome P450 3A (CYP3A). Inhibition of CYP3A-mediated metabolism by cobicistat increases the systemic exposure of CYP3A substrates atazanavir and darunavir.

12.2 Pharmacodynamics

Effects on Pharmacokinetic Enhancement

The effect of TYBOST on atazanavir pharmacokinetics was evaluated in the pharmacokinetic substudy (N=48) of Trial 114 in which participants with HIV-1 received atazanavir 300 mg coadministered with TYBOST 150 mg or atazanavir 300 mg coadministered with ritonavir 100 mg, both in combination with TRUVADA. The steady-state pharmacokinetic parameters of atazanavir were comparable when coadministered with TYBOST versus ritonavir groups as shown in Table 8 [see Clinical Studies (14.1)].

Table 8 Pharmacokinetic Parameters (Mean ± SD) of Atazanavir in Treatment-Naïve Adults with HIV-1 (Pharmacokinetic Substudy of Trial 114)
 | TYBOST + Atazanavir + TRUVADA Once Daily | Ritonavir + Atazanavir + TRUVADA Once Daily
Atazanavir Pharmacokinetic Parameters | N=22 | N=26
AUCtau (mcg∙hr/mL) | 46.13 ± 26.18 | 47.59 ± 24.38
Cmax (mcg/mL) | 3.91 ± 1.94 | 4.76 ± 1.94
Ctau (mcg/mL) | 0.80 ± 0.72 | 0.85 ± 0.72

The effect of TYBOST on darunavir was evaluated in a clinical study (Trial 115) in 31 healthy participants who received darunavir 800 mg in combination with TYBOST 150 mg or ritonavir 100 mg, all once daily, for 10 days. With the exception of Ctau, the steady-state pharmacokinetic parameters of darunavir were comparable when coadministered with TYBOST versus ritonavir as shown in Table 9, and these results were similar to those reported in previous clinical trials of darunavir 800 mg with ritonavir 100 mg once daily (refer to prescribing information for darunavir).

Table 9 Pharmacokinetic Parameters (Mean ± SD) of Darunavir in Healthy Adults (Trial 115)
 | TYBOST + Darunavir Once Daily | Ritonavir + Darunavir Once Daily
Darunavir Pharmacokinetic Parameters | N=31 | N=31
AUCtau (mcg∙hr/mL) | 81.08 ± 25.15 | 79.99 ± 27.20
Cmax (mcg/mL) | 7.74 ± 1.69 | 7.46 ± 1.52
C0h (mcg/mL) | 2.40 ± 1.22 | 2.48 ± 0.85
Ctau (mcg/mL) | 1.33 ± 0.89 | 1.87 ± 1.56

Cardiac Electrophysiology

In a thorough QT/QTc study in 48 healthy participants, a single dose of cobicistat 250 mg and 400 mg (1.67 and 2.67 times the dose in TYBOST) did not affect the QT/QTc interval. Prolongation of the PR interval was noted in participants receiving cobicistat. The maximum mean (95% upper confidence bound) difference in PR from placebo after baseline-correction was 9.5 (12.1) msec for the 250 mg cobicistat dose and 20.2 (22.8) for the 400 mg cobicistat dose.

Effects on Serum Creatinine

The effect of TYBOST on serum creatinine was investigated in a trial in participants with normal renal function (eGFR ≥80 mL/min, N=12) and mild-to-moderate renal impairment (eGFR 50–79 mL/min, N=18). A statistically significant decrease in the estimated glomerular filtration rate, calculated by Cockcroft-Gault method (eGFRCG) from baseline, was observed after 7 days of treatment with cobicistat 150 mg among participants with normal renal function (−9.9 ± 13.1 mL/min) and mild-to-moderate renal impairment (−11.9 ± 7.0 mL/min). No statistically significant changes in eGFRCG were observed compared to baseline for participants with normal renal function or mild-to-moderate renal impairment 7 days after cobicistat was discontinued. The actual glomerular filtration rate, as determined by the clearance of probe drug iohexol, was not altered from baseline following treatment with TYBOST among participants with normal renal function and mild-to-moderate renal impairment, indicating that cobicistat inhibits tubular secretion of creatinine, reflected as a reduction in eGFRCG, without affecting the actual glomerular filtration rate [see Warnings and Precautions (5.1)].

12.3 Pharmacokinetics

Absorption

In a trial where participants were instructed to take coadministered TYBOST and darunavir with food, median cobicistat peak plasma concentrations were observed approximately 3.5 hours postdose. Steady-state cobicistat Cmax, AUCtau, and Ctau (mean ± SD) values were 0.99 ± 0.3 mcg/mL (n=60), 7.6 ± 3.7 mcg∙hr/mL (n=59), and 0.03 ± 0.1 mcg/mL (n=59), respectively.

Effect of Food on Oral Absorption

A food-effect trial was not conducted for TYBOST. In clinical trials, TYBOST was coadministered with other antiretroviral agents [see Clinical Studies (14.1)] under fed conditions, in accordance with the prescribing information for these agents. It is recommended that TYBOST coadministered with atazanavir or darunavir be administered with food [see Dosage and Administration (2.1, 2.2)].

Distribution

Cobicistat is 97–98% bound to human plasma proteins and the mean blood-to-plasma ratio was approximately 0.5.

Metabolism

Cobicistat is metabolized by CYP3A and to a minor extent by CYP2D6 enzymes and does not undergo glucuronidation.

Elimination

The terminal plasma half-life of cobicistat following administration of TYBOST is approximately 3 to 4 hours. With single dose administration of [^14C] cobicistat after multiple dosing of cobicistat for 6 days, the mean percent of the administered dose excreted in feces and urine was 86.2% and 8.2%, respectively.

Specific Populations

Race and Gender

No clinically relevant differences in the pharmacokinetics of cobicistat were observed based on race or gender.

Pediatric Patients

In pediatric participants aged 12 to less than 18 years who received TYBOST 150 mg coadministered with atazanavir 300 mg (N=12), geometric mean atazanavir Cmax and AUCtau and cobicistat AUCtau values were approximately 20-30% higher than in adults and geometric mean atazanavir and cobicistat Ctau values were approximately 60% to 160% higher than in adults; the increases were not considered clinically significant. In pediatric participants aged 12 to less than 18 years who received TYBOST 150 mg coadministered with darunavir 800 mg (N=7), geometric mean darunavir Cmax and AUCtau values were similar between adults and adolescents. Geometric mean darunavir AUCtau and Ctau values were 15% and 32% lower, with geometric mean ratios of 0.85 (90% CI: 0.64, 1.13) and 0.68 (90% CI: 0.30, 1.55) in adolescent participants relative to adults, respectively. This difference was not considered clinically significant based on exposure-response relationships. Geometric mean cobicistat AUCtau, Cmax, and Ctau values were comparable in adolescents and adults (Table 10).

In pediatric participants aged 6 to less than 12 years (weighing ≥25 kg to <40 kg) who received TYBOST 150 mg coadministered with atazanavir (N=14) or darunavir (N=9), AUCtau and Cmax values were similar to those in adults, while the Ctrough was 33% higher for atazanavir and 44% higher for darunavir than in adults. In this study, exposures of cobicistat (AUCtau, Cmax, and Ctrough) in the combined groups were 88%, 52%, and 192%, respectively, higher than in adults (Table 10). However, the increases were not considered clinically significant.

In pediatric participants at least 2 years of age (weighing ≥14 kg to <25 kg) who received TYBOST 90 mg coadministered with atazanavir (N=15) or darunavir (N=11), exposures (AUCtau, Cmax, and Ctrough) were higher for atazanavir (46%, 72% and 42%, respectively) and darunavir (49%, 88%, and 66%, respectively) as compared to exposures in adults. Exposures of cobicistat (AUCtau, Cmax, and Ctrough) in the combined groups were 58%, 29%, and 126%, respectively, higher than in adults (Table 10). However, the increases were not considered clinically significant.

Table 10 Multiple-Dose PK Parameters of Cobicistat, Atazanavir, and Darunavir Following Administration of TYBOST with Atazanavir or Darunavir in Pediatric Participants with HIV-1 Weighing at Least 14 kg [From Intensive PK analysis of Trial 128.]
Parameter Mean (CV%) | Cobicistat |  | Atazanavir | Darunavir
Treatment Administered | TYBOST + Atazanavir | TYBOST + Darunavir | TYBOST + Atazanavir | TYBOST + Darunavir
Pediatric Participants 12 to less than 18 years of age (weighing ≥35 kg), [Values are geometric means] | N=12 | N=7 | N=12 | N=7
AUCtau (mcg∙hr/mL) | 12.11 (44.7) | 8.33 (34.9) | 49.48 (49.1) | 77.22 (29.5)
Cmax (mcg/mL) | 1.28 (31.7) | 1.10 (20.0) | 4.32 (49.9) | 7.32 (21.7)
Ctau (mcg/mL) | 0.09 (156.2) | 0.02 (123.9) [N=5; Data from two participants who had undetectable TYBOST Ctau concentrations were excluded from summary statistics.] | 0.91 (96.4) | 0.68 (91.6)
Pediatric Participants 6 to less than 12 years of age (weighing ≥25 to < 40 kg), [Values are arithmetic means] | N=14 | N=9 | N=14 | N=9
AUCtau (mcg∙hr/mL) | 21.03 (21.7) [N=13] | 13.67 (39.8) | 47.48 (38.4) | 110.51 (30.8)
Cmax (mcg/mL) | 2.62 (20.5) | 1.64 (29.8) | 4.19 (38.9) | 9.10 (23.9)
Ctau (mcg/mL) | 0.10 (118.4) | 0.06 (109.7) | 0.92 (66.4) | 3.78 (43.2)
Pediatric Participants at least 2 years of age (weighing ≥14 to < 25 kg), | N=15 | N=11 | N=15 | N=11
AUCtau (mcg∙hr/mL) | 15.14 (39.3) | 16.07 (46.9) | 65.51 (50.8) | 160.53 (54.0)
Cmax (mcg/mL) | 1.95 (37.1) | 2.08 (36.0) | 6.78 (52.0) | 15.02 (38.0)
Ctau (mcg/mL) | 0.06 (114.0) | 0.06 (138.6) | 0.95 (58.0) | 2.79 (92.1)
Adults [From pooled Intensive PK analysis of trials with TYBOST + atazanavir.] , [From Intensive PK analysis of Trial GS-US-299-0102 with TYBOST + darunavir.] , | N=30 | N=21 | N=30 | N=21
AUCtau (mcg∙hr/mL) | 9.65 (41.8) | 7.69 (43.9) | 39.96 (52.1) | 90.56 (45.3)
Cmax (mcg/mL) | 1.28 (35.6) | 1.04 (35.3) | 3.54 (45.8) | 8.34 (33.3)
Ctau (mcg/mL) | 0.04 (112.7) | 0.02 (135.1) [N=18.] | 0.58 (84.7) | 1.00 (108.0)
CV=Coefficient of Variation

Patients with Renal Impairment

No clinically relevant differences in cobicistat pharmacokinetics were observed between participants with severe renal impairment (estimated creatinine clearance below 30 mL/min) and healthy participants [see Use in Specific Populations (8.6)].

Patients with Hepatic Impairment

No clinically relevant differences in cobicistat pharmacokinetics were observed between participants with moderate hepatic impairment (Child-Pugh Class B) and healthy participants. The effect of severe hepatic impairment (Child-Pugh Class C) on the pharmacokinetics of cobicistat has not been studied [see Use in Specific Populations (8.7)].

Pregnancy and Postpartum

The exposure to total and unbound darunavir boosted with cobicistat after intake of darunavir/cobicistat as part of an antiretroviral regimen was substantially lower during the second and third trimesters of pregnancy compared with 6–12 weeks postpartum (see Table 11 and Figure 1).

Table 11: Pharmacokinetic Results of Total Darunavir after Administration of Darunavir/Cobicistat Once Daily as Part of an Antiretroviral Regimen, During the 2nd Trimester of Pregnancy, the 3rd Trimester of Pregnancy, and Postpartum
Pharmacokinetics of total darunavir (mean ± SD) | 2nd Trimester of pregnancy N=7 | 3rd Trimester of pregnancy N=6 | Postpartum (6–12 weeks) N=6
Cmax, ng/mL | 4,340 ± 1,616 | 4,910 ± 970 | 7,918 ± 2,199
AUC24h, ng.h/mL | 47,293 ± 19,058 | 47,991 ± 9,879 | 99,613 ± 34,862
Cmin, ng/mL | 168 ± 149 | 184 ± 99 | 1,538 ± 1,344

Figure 1: Pharmacokinetic Results (Within-participant Comparison) of Total and Unbound Darunavir and Total Cobicistat After Administration of Darunavir/Cobicistat at 800/150 mg Once Daily as Part of an Antiretroviral Regimen, During the 2nd and 3rd Trimester of Pregnancy Compared to Postpartum

Legend: 90% CI: 90% confidence interval; GMR: geometric mean ratio (i.e. second or third trimester / postpartum). Solid vertical line: ratio of 1.0; dotted vertical lines: reference lines of 0.8 and 1.25.

Assessment of Drug Interactions

Drug interaction trials were conducted with TYBOST (as a single entity) and desipramine, digoxin, and efavirenz. Drug interaction trials of TYBOST coadministered with atazanavir or darunavir included atorvastatin, drospirenone/ethinyl estradiol, and rosuvastatin. Drug interaction trials of TYBOST coadministered with elvitegravir included rosuvastatin and rifabutin.

The effects of cobicistat on the exposure of coadministered drugs are shown in Table 12.

Table 12 Drug Interactions: Changes in Pharmacokinetic Parameters for Coadministered Drugs in the Presence of Cobicistat [All interaction studies conducted in healthy participants.]
Note: The information listed below is not a comprehensive list of all the available drug interaction data for concomitant medications with cobicistat containing regimens. Please refer to the U.S. prescribing information for antiretroviral medications administered in combination with cobicistat for additional drug interaction information.
Coadministered Drug | Dose of Coadministered Drug (mg) | TYBOST Dose (mg) | N | Mean Ratio of Coadministered Drug Pharmacokinetic Parameters (90% CI); No effect = 1.00
Coadministered Drug | Dose of Coadministered Drug (mg) | TYBOST Dose (mg) | N | Cmax | AUC
Atorvastatin | 10 single dose | 150 once daily | 16 | 18.85 [Study conducted in the presence of 300 mg atazanavir.] (13.53, 26.27) | 9.22 (7.58, 11.22)
Atorvastatin | 10 single dose | 150 once daily | 16 | 4.19 [Study conducted in the presence of 800 mg darunavir.] (3.67, 4.78) | 3.90 (3.52, 4.32)
Desipramine | 50 single dose | 150 once daily | 8 | 1.24 (1.08, 1.44) | 1.65 (1.36, 2.02)
Digoxin | 0.5 single dose | 150 once daily | 22 | 1.41 (1.29, 1.55) | 1.08 (1.00, 1.17)
Drospirenone/ ethinyl estradiol | 3 drospirenone single dose | 150 once daily | 14 | 1.12 (1.05, 1.19) | 2.30 (2.00, 2.64)
Drospirenone/ ethinyl estradiol | 0.02 ethinyl estradiol single dose | 150 once daily | 14 | 0.82 (0.76, 0.89) | 0.78 (0.73, 0.85)
Drospirenone/ ethinyl estradiol | 3 drospirenone single dose | 150 once daily | 15 | 1.15 (1.05, 1.26) | 1.58 (1.47, 1.71)
Drospirenone/ ethinyl estradiol | 0.02 ethinyl estradiol single dose | 150 once daily | 15 | 0.86 (0.77, 0.95) | 0.70 (0.63, 0.77)
Efavirenz | 600 single dose | 150 once daily | 17 | 0.87 (0.80, 0.94) | 0.93 (0.89, 0.97)
Rosuvastatin | 10 single dose | 150 once daily | 16 | 10.58 (8.72, 12.83) | 3.42 (2.87, 4.07)
Rosuvastatin | 10 single dose | 150 once daily | 16 | 3.77 (3.29, 4.32) | 1.93 (1.70, 2.20)

12.4 Microbiology

Antiviral Activity

Cobicistat does not inhibit recombinant HIV-1 protease in a biochemical assay and has no detectable antiviral activity in cell culture against HIV-1, HBV, or HCV. The antiviral activity in cell culture of selected HIV-1 antiretroviral drugs was not antagonized by cobicistat.

Resistance

In an analysis of treatment-failure adult participants who received TYBOST coadministered with atazanavir and TRUVADA in Trial 114 through Week 144, evaluable genotypic data from paired baseline and treatment-failure isolates from participants who had HIV-1 RNA greater than or equal to 400 copies/mL were available for all 21 virologic failures in the TYBOST group (6%, 21/344). Among the 21 participants, 3 developed the emtricitabine resistance-associated substitution M184V. No participant developed the tenofovir resistance-associated substitution K65R or K70E, or any primary resistance substitution associated with protease inhibitors. In the ritonavir group, evaluable genotypic data were available for all 19 virologic failures (5%, 19/348). Among the 19 participants, 1 developed the emtricitabine resistance-associated substitution M184V with no tenofovir or protease inhibitor resistance-associated substitutions.

13 NONCLINICAL TOXICOLOGY

13.1 Carcinogenesis, Mutagenesis, Impairment of Fertility

Carcinogenesis

In a long-term carcinogenicity study in mice, no drug-related increases in tumor incidence were observed at doses up to 50 and 100 mg/kg/day (males and females, respectively). Cobicistat exposures at these doses were approximately 7 (male) and 16 (females) times, respectively, the human systemic exposure at the therapeutic daily dose. In a long-term carcinogenicity study of cobicistat in rats, an increased incidence of follicular cell adenomas and/or carcinomas in the thyroid gland was observed at doses of 25 and 50 mg/kg/day in males, and at 30 mg/kg/day in females. The follicular cell findings are considered to be rat-specific, secondary to hepatic microsomal enzyme induction and thyroid hormone imbalance, and are not relevant for humans. At the highest doses tested in the rat carcinogenicity study, systemic exposures were approximately 2 times the human systemic exposure at the therapeutic daily dose.

Mutagenesis

Cobicistat was not genotoxic in the reverse mutation bacterial test (Ames test), mouse lymphoma, or rat micronucleus assays.

Impairment of Fertility

Cobicistat did not affect fertility in male or female rats at daily exposures (AUC) approximately 3-fold higher than human exposures at the recommended 150 mg daily dose.

Fertility was normal in the offspring of rats exposed daily from before birth (in utero) through sexual maturity at daily exposures (AUC) of approximately similar human exposures at the recommended 150 mg daily dose.

14 CLINICAL STUDIES

14.1 Clinical Trial Results in Treatment-Naïve Adult Participants with HIV-1 – Trial 114

The activity of TYBOST as a CYP3A inhibitor to increase the systemic exposures of atazanavir or darunavir has been demonstrated in pharmacokinetic trials. In these trials, the exposure of atazanavir or darunavir coadministered with TYBOST 150 mg was consistent with those observed with ritonavir 100 mg [see Clinical Pharmacology (12.2)]. For clinical efficacy of darunavir/ritonavir 800/100 mg once daily, refer to the prescribing information for darunavir.

The safety and efficacy of TYBOST coadministered with atazanavir were evaluated in a randomized, double-blind, active-controlled trial (Trial 114) in treatment-naïve participants with HIV-1 and baseline estimated creatinine clearance above 70 mL/min (N=692). In Trial 114, participants were randomized in a 1:1 ratio to receive either atazanavir 300 mg + TYBOST 150 mg once daily or atazanavir 300 mg + ritonavir 100 mg once daily. All participants received concomitant treatment with 300 mg of TDF and 200 mg of emtricitabine once a day administered as single tablet TRUVADA. Randomization was stratified by screening HIV-1 RNA level (≤100,000 copies/mL or >100,000 copies/mL).

The mean age of participants was 37 years (range 19–70); 83% were male, 60% were White, 18% were Black, and 12% were Asian. The mean baseline plasma HIV-1 RNA was 4.8 log10 copies/mL (range 3.2–6.4). Forty percent of patients had baseline viral loads >100,000 copies/mL. The mean baseline CD4+ cell count was 352 cells/mm^3 (range 1–1455) and 17% had CD4+ cell counts ≤200 cells/mm^3.

Virologic outcomes in Trial 114 through Week 144 are presented in Table 13. In Trial 114, the mean increase from baseline in CD4+ cell count at Week 144 was 281 cells/mm^3 in the TYBOST group and 297 cells/mm^3 in the ritonavir group.

Table 13 Virologic Outcome of Randomized Treatment of Trial 114 in Treatment Naïve Adults with HIV-1 at Week 144 [Week 144 window was between Day 967 and 1050 (inclusive).]
 | TYBOST + Atazanavir + TRUVADA (N=344) | Ritonavir + Atazanavir + TRUVADA (N=348)
HIV-1 RNA <50 copies/mL | 72% | 74%
Treatment Difference | −2.1% (95% CI = −8.7%, 4.5%)
HIV RNA ≥50 copies/mL [Included participants who had ≥50 copies/mL in the Week 144 window; participants who discontinued early due to lack or loss of efficacy; participants who discontinued for reasons other than an adverse event (AE), death, or lack or loss of efficacy and at the time of discontinuation had a viral value of ≥50 copies/mL.] | 8% | 5%
No Virologic Data at Week 144 Window | 20% | 21%
Discontinued Study Drug Due to AE or Death [Includes participants who discontinued due to AE or death at any time point from Day 1 through the time window if this resulted in no virologic data on treatment during the specified window.] | 11% | 11%
Discontinued Study Drug Due to Other Reasons and Last Available HIV-1 RNA <50 copies/mL [Includes participants who discontinued for reasons other than an AE, death, or lack or loss of efficacy; e.g., withdrew consent, lost to follow-up, etc.] | 8% | 10%
Missing Data During Window but on Study Drug | <1% | <1%

14.2 Clinical Trial Results in Pediatric Participants with HIV-1 – Trial 128

Trial 128 was a Phase 2/3 multicenter, open-label trial to evaluate the pharmacokinetics, safety, and efficacy of TYBOST coadministered with atazanavir or darunavir in pediatric participants with HIV-1 and baseline estimated creatinine clearance ≥90 mL/min/1.73 m^2, including virologically-suppressed pediatric participants between the ages of 12 to less than 18 years (cohort 1 [Part A], N=22), pediatric participants between the ages of 6 to less than 12 years (cohort 2, N=23, 9 of whom switched to TYBOST co-administered with darunavir and were all virologically-suppressed at baseline), and pediatric participants at least 2 years of age (cohort 3, N=26, 11 of whom switched to TYBOST co-administered with darunavir and were all virologically-suppressed at baseline). Participants in cohort 1 (Part A) were on a stable antiretroviral regimen (for at least 3 months), consisting of atazanavir or darunavir, both administered with ritonavir combined with 2 NRTIs or consisting of a third agent administered with 2 NRTIs (cohorts 2 and 3 only). TYBOST 150 mg was given once daily with atazanavir or darunavir in cohort 1 (Part A) and cohort 2. TYBOST 90 mg was given once daily with atazanavir or darunavir in cohort 3. For all cohorts, participants were administered a background regimen containing 2 NRTIs.

Cohort 1 (Part A): 12 to <18 years; ≥35 kg

In cohort 1 (Part A), the mean age of participants was 14 years (range 12 to 17 years); median weight was 55 kg; 62% were male, 38% were Asian, 33% were White, 19% were Black, and 67% were not Hispanic or Latino. At baseline, 20/21 participants had plasma HIV-1 RNA <50 copies/mL and 1 participant had plasma HIV-1 RNA of 50 copies/mL.

In participants who switched to TYBOST coadministered with atazanavir, 93% (13/14) of participants were suppressed (HIV-1 RNA <50 copies/mL) at Week 48 and 1 evaluable participant experienced virologic failure at Week 24 without significant emergent resistance associated substitutions in reverse transcriptase or protease. From a median baseline CD4+ cell count and CD4+% of 770 cells/mm^3 (range 486 to 1765 cells/mm^3) and 33% (range 23% to 45%), respectively, the median change from baseline in CD4+ cell count and CD4+% at Week 48 was -60 cells/mm^3 (range -500 to 705 cells/mm^3) and -0.3% (range -6% to 8%), respectively.

In participants who switched to TYBOST coadministered with darunavir, 86% (6/7) of participants remained suppressed (HIV-1 RNA <50 copies/mL), and 1 subject had missing data at Week 48. From a median baseline CD4+ cell count and CD4+% of 1117 cells/mm^3 (range 658 to 2416 cells/mm^3) and 45% (range 28% to 56%), respectively, the median change from baseline in CD4+ cell count and CD4+% at Week 48 was -342 cells/mm^3 (range -1389 to 219 cells/mm^3) and -6% (range -12% to 5%), respectively. All 6 participants with available data had CD4+ cell counts above 800 cells/mm^3 at Week 48.

Cohort 2: 6 to <12 years; ≥25 kg to <40 kg

Participants in cohort 2 who switched to TYBOST coadministered with darunavir (n=9) had a mean age of 10 years (range 9 to 11 years); median weight was 29 kg; 11% were male, and 89% were Black. At baseline, all participants had plasma HIV-1 RNA <50 copies/mL.

In these participants who switched to TYBOST coadministered with darunavir, 100% (9/9) of participants remained suppressed (HIV-1 RNA <50 copies/mL) at Week 48. From a mean (SD) baseline CD4+ count of 898 (209), the mean (SD) change from baseline in CD4+ cell count was 10 (199) cells/mm^3 and the mean (SD) change in CD4% was 1.26% (6.2%) at Week 48.

Cohort 3: ≥2 years; ≥14 kg to <25 kg

Participants in cohort 3 who switched to TYBOST coadministered with darunavir (n=11) had a mean age of 5 years (range 3 to 7 years); median weight was 17 kg; 45% were male, and 100% were Black. At baseline, all participants had plasma HIV-1 RNA <50 copies/mL.

In these participants who switched to TYBOST coadministered with darunavir, 91% (10/11) of participants remained suppressed (HIV-1 RNA <50 copies/mL) at Week 48. From a mean (SD) CD4+ count of 1185 (317), the mean (SD) change from baseline in CD4+ cell count was -122 (329) cells/mm^3 and the mean (SD) change in CD4% was 1.4% (2.5%) at Week 48.

16 HOW SUPPLIED/STORAGE AND HANDLING

TYBOST tablets are available in bottles containing 30 tablets and a silica gel desiccant, with a child-resistant closure.

STORAGE AND HANDLING

- TYBOST tablets, 150 mg, are orange, round, biconvex, film-coated, and debossed with “GSI” on one side and plain faced on the other side. (NDC 61958-1401-1).
- TYBOST tablets, 90 mg, are white, round, biconvex, film-coated, and debossed with “TYB” on one side and “90” on the other side. (NDC 61958-1402-1).

Store at 25 °C (77 °F); excursions permitted to 15°C –30 °C (59–86 °F) (see USP Controlled Room Temperature).

- Keep container tightly closed.
- Dispense only in original container.
- Do not use if seal over bottle opening is broken or missing.

17 PATIENT COUNSELING INFORMATION

Advise the patient to read the FDA-approved patient labeling (Patient Information).

Drug Interaction

Inform patients that TYBOST coadministered with atazanavir or darunavir may interact with many drugs with potential serious implications and that some drugs are contraindicated with TYBOST coadministered with atazanavir or darunavir. Advise patients to report to their healthcare provider the use of any other prescription or nonprescription medication, including acid-modifying medications or herbal products, including St. John's wort [see Contraindications (4), Warnings and Precautions (5.3), and Drug Interactions (7)].

New Onset or Worsening Renal Impairment

Inform patients that renal impairment, including cases of acute renal failure and Fanconi syndrome, has been reported when TYBOST is used in combination with a TDF containing regimen [see Warnings and Precautions (5.2)].

Pregnancy

Advise patients that TYBOST is not recommended during pregnancy and to alert their healthcare provider if they get pregnant while taking TYBOST [see Use in Specific Populations (8.1)].

Inform patients that there is a pregnancy exposure registry that monitors fetal outcomes in pregnant individuals exposed to TYBOST during pregnancy [see Use in Specific Populations (8.1)].

Lactation

Inform individuals with HIV-1 infection that the potential risks of breastfeeding include: (1) HIV-1 transmission to HIV-1–negative infants, (2) developing viral resistance in HIV-1–positive infants, and (3) adverse reactions in a breastfed infant similar to those seen in adults [see Use in Specific Populations (8.2)].

Dosing Instructions

Inform patients that TYBOST must be taken at the same time as atazanavir or darunavir and with food once daily as prescribed. It is important to take TYBOST and atazanavir or darunavir together on a regular dosing schedule and to avoid missing doses. Counsel patients about the risks of developing resistance to their HIV-1 medications.

© 2025 Gilead Sciences, Inc. All rights reserved.

TYBOST, GSI, and TRUVADA are trademarks of Gilead Sciences, Inc., or its related companies. All other trademarks are the property of their respective owners.

Patient Information
TYBOST® (TYE-bost)
(cobicistat)
tablets

Important: Ask your healthcare provider or pharmacist about medicines that should not be taken with TYBOST. For more information, see the section “What should I tell my healthcare provider before taking TYBOST?”
Also read the Patient Information for atazanavir or darunavir prescribed by your healthcare provider when taking TYBOST.

What is TYBOST?
TYBOST is a prescription medicine used in adults and children who weigh at least 31 pounds (14 kg):

- 1 time each day with the Human Immunodeficiency Virus-1 (HIV-1) medicines atazanavir or darunavir, to increase the amount of those medicines in your blood.
- TYBOST is not an HIV-1 medicine and does not treat the HIV-1 virus. You must also take all the HIV-1 medicines prescribed by your healthcare provider even if you take TYBOST and atazanavir or darunavir.
- TYBOST should not be used if you take darunavir when prescribed by your healthcare provider to be taken 2 times each day, or if you take other HIV-1 protease inhibitor medicines, including fosamprenavir, saquinavir, or tipranavir.

It is not known if TYBOST when taken with atazanavir is safe and effective in children who weigh less than 31 pounds (14 kg) of if TYBOST when taken with darunavir is safe and effective in children who weigh less than 33 pounds (15 kg).

Do not take TYBOST combined with atazanavir or darunavir if you also take a medicine that contains:

- alfuzosin hydrochloride
- carbamazepine
- colchicine, if you have liver or kidney problems
- dronedarone hydrochloride
- ergot-containing medicines:
  - dihydroergotamine mesylate
  - ergotamine tartrate
  - methylergonovine maleate
- lomitapide
- lovastatin
- lurasidone

- midazolam, when taken by mouth
- phenobarbital
- phenytoin
- pimozide
- ranolazine
- rifampin
- sildenafil, when used for treating the lung problem pulmonary arterial hypertension (PAH)
- simvastatin
- St. John’s wort (Hypericum perforatum) or a product that contains St. John’s wort
- triazolam

Do not take TYBOST with atazanavir if you also take a medicine that contains:

- drospirenone/ethinyl estradiol
- indinavir
- irinotecan
- nevirapine

Before you take TYBOST, tell your healthcare provider about all of your medical conditions, including if you:

- have kidney problems
- have liver problems
- are pregnant or plan to become pregnant. It is not known if TYBOST can harm your unborn baby.
  - TYBOST should not be used during pregnancy because you may not have enough TYBOST in your body during pregnancy.
  - TYBOST may reduce how well some hormonal birth control (contraceptives) works. You should consider using a different form of birth control or an additional barrier method of birth control during treatment with TYBOST.
  - Tell your healthcare provider if you become pregnant during treatment with TYBOST. Your healthcare provider may prescribe different medicines if you become pregnant during treatment with TYBOST.
  Pregnancy Registry: There is a pregnancy registry for people who take TYBOST during pregnancy. The purpose of the registry is to collect information about the health of you and your baby. Talk to your healthcare provider about how you can take part in this registry.
- are breastfeeding or plan to breastfeed. It is not known if TYBOST can pass to your baby in your breast milk.
  Talk to your healthcare provider about the following risks to your baby from breastfeeding during treatment with TYBOST:
  - the HIV-1 virus may pass to your baby if your baby does not have HIV-1.
  - the HIV-1 virus may become harder to treat if your baby has HIV-1.
  - your baby may get side effects from TYBOST.

Tell your healthcare provider about all the medicines you take, including prescription and over-the-counter medicines, antacids, vitamins, and herbal supplements. TYBOST with atazanavir or darunavir may affect the way other medicines work, and other medicines may affect how TYBOST with atazanavir or darunavir works. Taking TYBOST with atazanavir or darunavir, along with certain other medicines can lead to severe or life-threatening side effects, or could lead to death. Keep a list of your medicines and show it to your healthcare provider and pharmacist when you get a new medicine.

- You can ask your healthcare provider or pharmacist for a list of medicines that interact when taken with TYBOST with atazanavir or darunavir.
- Do not start a new medicine without telling your healthcare provider. Your healthcare provider can tell you if it is safe to take TYBOST with atazanavir or darunavir, along with other medicines.

How should I take TYBOST?

- Take TYBOST exactly as your healthcare provider tells you.
- Do not change your dose or stop taking TYBOST without first talking with your healthcare provider.
- Stay under the care of your healthcare provider during treatment with TYBOST. See your healthcare provider regularly during treatment with TYBOST.
- Take TYBOST 1 time each day at the same time you take atazanavir or darunavir. It is important to take these medicines on a regular dosing schedule.
- Take TYBOST with atazanavir or TYBOST with darunavir, along with food.
- If you take too much TYBOST, call your healthcare provider or go to the nearest hospital emergency room right away.
- Do not run out of TYBOST. The virus in your blood may become resistant to the HIV-1 medicine atazanavir or darunavir if TYBOST is stopped for even a short time. When your supply starts to run low, get more from your healthcare provider or pharmacy.

What are the possible side effects of TYBOST?
TYBOST may cause serious side effects, including:

- Kidney problems. TYBOST when taken with certain other medicines can cause new or worse kidney problems, including kidney failure. Your healthcare provider should do blood and urine tests to check your kidneys before you start and during treatment with TYBOST.

The most common side effects of TYBOST with atazanavir include: yellowing of the skin or the whites of your eyes and rash.
These are not all the possible side effects of TYBOST.
Call your doctor for medical advice about side effects. You may report side effects to FDA at 1-800-FDA-1088.

How should I store TYBOST?

- Store TYBOST at room temperature between 68°F to 77°F (20°C to 25°C).
- TYBOST comes in a child-resistant container.
- Do not use TYBOST if the seal over the bottle opening is broken or missing.
- Keep TYBOST in its original container.
- Keep the container tightly closed.

Keep TYBOST and all medicines out of reach of children.

General information about the safe and effective use of TYBOST.
Medicines are sometimes prescribed for purposes other than those listed in a Patient Information leaflet. Do not use TYBOST for a condition for which it was not prescribed. Do not give TYBOST to other people, even if they have the same symptoms you have. It may harm them. You can ask your pharmacist or healthcare provider for information about TYBOST that is written for health professionals.

What are the ingredients in TYBOST?
Active ingredient: cobicistat
Inactive ingredients: silicon dioxide, microcrystalline cellulose, croscarmellose sodium, and magnesium stearate. The 150 mg tablets are film-coated with a coating material containing polyethylene glycol, polyvinyl alcohol, talc, titanium dioxide, sunset yellow FCF (FD&C Yellow #6) aluminum lake, and iron oxide yellow. The 90 mg tablets are film-coated with a coating material containing polyvinyl alcohol, titanium dioxide, polyethylene glycol, and talc.
Manufactured and distributed by: Gilead Sciences, Inc. Foster City, CA 94404 © 2021 Gilead Sciences, Inc. All rights reserved.
TYBOST, GSI, and TRUVADA are trademarks of Gilead Sciences, Inc., or its related companies. All other trademarks are the property of their respective owners.
203094-GS-011
For more information, call 1-800-445-3235 or go to www.GILEAD.com

This Patient Information has been approved by the U.S. Food and Drug Administration.

Revised: 06/2025

PRINCIPAL DISPLAY PANEL - 150 mg Tablet Bottle Label

NDC 61958-1401-1
30 tablets

Tybost®
(cobicistat) tablets

150 mg

Rx only

Note to pharmacist:
Do not cover ALERT box with pharmacy label.

ALERT: Find out about medicines that
should NOT be taken with Tybost

PRINCIPAL DISPLAY PANEL - 90 mg Tablet Bottle Label

NDC 61958-1402-1
30 tablets

Tybost®
(cobicistat) tablets

90 mg

Note to pharmacist:
Do not cover ALERT box
with pharmacy label.

ALERT: Find out about medicines that
should NOT be taken with Tybost

Rx only